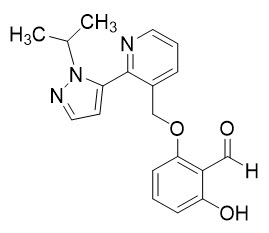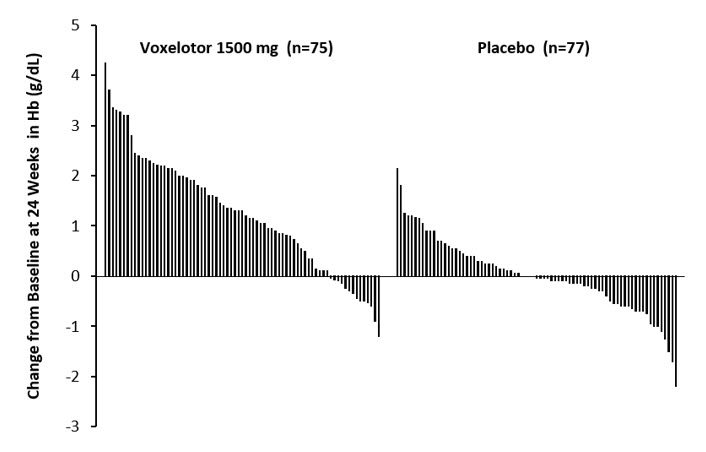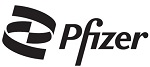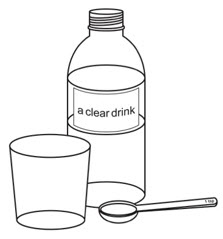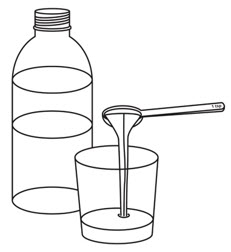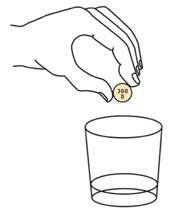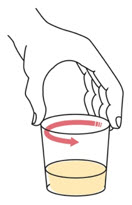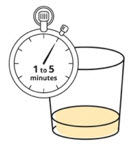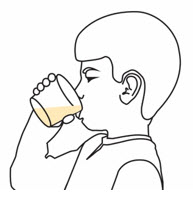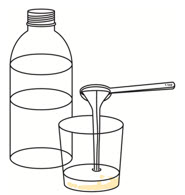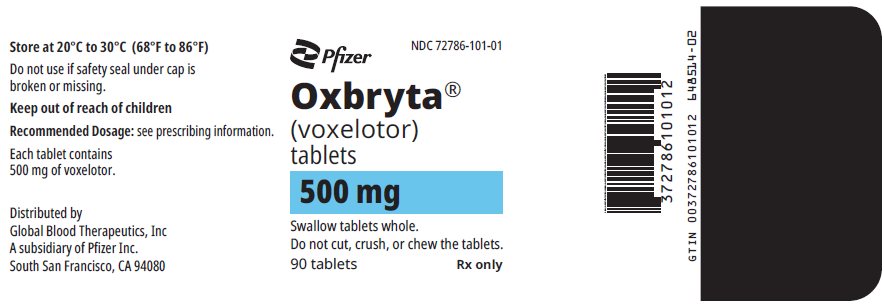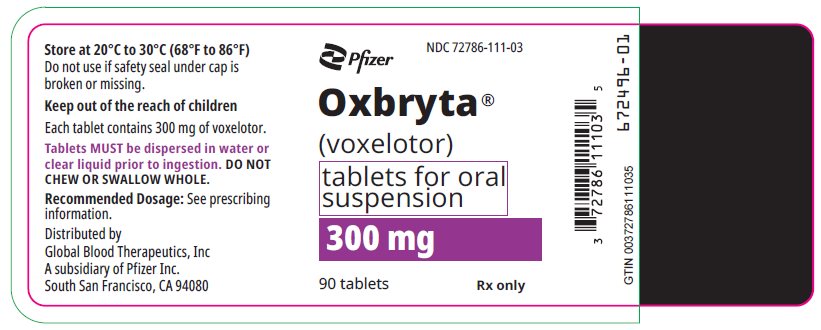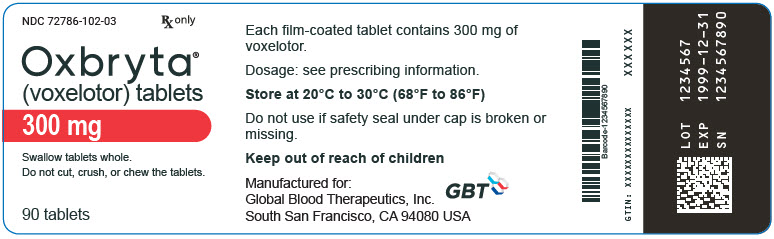 DRUG LABEL: OXBRYTA
NDC: 72786-101 | Form: TABLET, FILM COATED
Manufacturer: Global Blood Therapeutics, Inc, A subsidiary of Pfizer Inc.
Category: prescription | Type: HUMAN PRESCRIPTION DRUG LABEL
Date: 20231226

ACTIVE INGREDIENTS: Voxelotor 500 mg/1 1
INACTIVE INGREDIENTS: Microcrystalline Cellulose; Croscarmellose Sodium; Sodium Lauryl Sulfate; SILICON DIOXIDE; magnesium stearate; Polyethylene glycol 3350; POLYVINYL ALCOHOL, UNSPECIFIED; talc; Titanium dioxide; FERRIC OXIDE YELLOW

HIGHLIGHTS OF PRESCRIBING INFORMATION

These highlights do not include all the information needed to use OXBRYTA safely and effectively. See full prescribing information for OXBRYTA.
OXBRYTA® (voxelotor) tablets, for oral use
OXBRYTA® (voxelotor) tablets for oral suspension
Initial U.S. Approval: 2019

RECENT MAJOR CHANGES

Dosage and Administration (2) | 10/2022
Warnings and Precautions, Hypersensitivity Reactions (5.1) | 08/2023

1 INDICATIONS AND USAGE

OXBRYTA is a hemoglobin S polymerization inhibitor indicated for the treatment of sickle cell disease in adults and pediatric patients 4 years of age and older.
This indication is approved under accelerated approval based on increase in hemoglobin (Hb). Continued approval for this indication may be contingent upon verification and description of clinical benefit in confirmatory trial(s). (1)

2 DOSAGE AND ADMINISTRATION

OXBRYTA can be taken with or without food. (2.7)

Recommended dosage:

- Adults and pediatric patients 12 years and older: 1,500 mg orally once daily. (2.1)
- Pediatric patients 4 to less than 12 years: Dosing with OXBRYTA is based on body weight. See Table 1 for complete dosing recommendations. (2.2)

Recommended dosage for severe hepatic impairment (Child Pugh C):

- Adults and pediatric patients 12 years and older: 1,000 mg orally once daily. (2.3)
- Pediatric patients 4 to less than 12 years: Reduce the dose of OXBRYTA based on body weight. See Table 2 for complete dosing recommendations. (2.4)

3 DOSAGE FORMS AND STRENGTHS

- Tablets: 300 mg and 500 mg (3)
- Tablets for oral suspension: 300 mg (3)

4 CONTRAINDICATIONS

Prior drug hypersensitivity to voxelotor or excipients. (4)

5 WARNINGS AND PRECAUTIONS

- Hypersensitivity Reactions: Observe for signs and symptoms and manage promptly. (5.1)
- Laboratory Test Interference: Perform quantification of hemoglobin species when patient is not receiving OXBRYTA. (5.2)

6 ADVERSE REACTIONS

Most common adverse reactions (incidence ≥10% with a difference of >3% compared to placebo) are headache, diarrhea, abdominal pain, nausea, rash, and pyrexia. (6.1)
Most common adverse reactions (incidence >10%) reported in pediatric patients 4 to <12 years are pyrexia, vomiting, rash, abdominal pain, diarrhea, and headache. (6.1)

To report SUSPECTED ADVERSE REACTIONS, contact Pfizer Inc. at 1-800-438-1985 or FDA at 1-800-FDA-1088 or www.fda.gov/medwatch.

7 DRUG INTERACTIONS

- Sensitive CYP3A4 Substrates: Avoid coadministration of sensitive CYP3A4 substrates with a narrow therapeutic index. (7.2)
- Strong or moderate CYP3A4 Inducers: Avoid coadministration with strong or moderate CYP3A4 inducers. If unavoidable, increase the dose of OXBRYTA. (2.5, 2.6, 7.1)

8 USE IN SPECIFIC POPULATIONS

Lactation: Advise not to breastfeed. (8.2)

FULL PRESCRIBING INFORMATION

1 INDICATIONS AND USAGE

OXBRYTA is indicated for the treatment of sickle cell disease (SCD) in adults and pediatric patients 4 years of age and older.

This indication is approved under accelerated approval based on increase in hemoglobin (Hb) [see Clinical Studies (14)]. Continued approval for this indication may be contingent upon verification and description of clinical benefit in confirmatory trial(s).

2 DOSAGE AND ADMINISTRATION

2.1 Recommended Dosage for Adults and Pediatric Patients 12 Years and Older

The recommended dosage of OXBRYTA is 1,500 mg orally once daily.

2.2 Recommended Dosage for Pediatric Patients 4 Years to Less Than 12 Years

For pediatric patients 4 years to less than 12 years, select the appropriate product (OXBRYTA tablets or OXBRYTA tablets for oral suspension) based on patient's ability to swallow tablets and patient's weight.

The recommended dosage of OXBRYTA for pediatric patients 4 years to less than 12 years is shown in Table 1.

Table 1: Recommended OXBRYTA Dosage in Pediatric Patients 4 Years to Less Than 12 Years
Body Weight | Recommended Dose (once daily)
40 kg or greater | 1,500 mg
20 kg to less than 40 kg | 900 mg
10 kg to less than 20 kg | 600 mg

2.3 Recommended Dosage for Adults and Pediatric Patients 12 Years and Older with Hepatic Impairment

The recommended dosage of OXBRYTA in adults and pediatric patients 12 years and older with severe hepatic impairment (Child Pugh C) is 1,000 mg orally once daily.

No dosage adjustment of OXBRYTA is required for patients with mild or moderate hepatic impairment [see Use in Specific Populations (8.6) and Clinical Pharmacology (12.3)].

2.4 Recommended Dosage for Pediatric Patients 4 Years to Less Than 12 Years with Hepatic Impairment

The recommended dosage of OXBRYTA in pediatric patients 4 years to less than 12 years with severe hepatic impairment (Child Pugh C) is described in Table 2.

No dosage adjustment of OXBRYTA is required for patients with mild or moderate hepatic impairment [see Use in Specific Populations (8.6) and Clinical Pharmacology (12.3)].

Table 2: Recommended OXBRYTA Dosage in Pediatric Patients 4 Years to Less Than 12 Years with Severe Hepatic Impairment (Child Pugh C)
Body Weight | Recommended Dose (once daily)
40 kg or greater | 1,000 mg (two 500 mg tablets) or 900 mg (three 300 mg tablets for oral suspension or three 300 mg tablets)
20 kg to less than 40 kg | 600 mg
10 kg to less than 20 kg | 300 mg

2.5 Recommended Dosage of OXBRYTA for Adults and Pediatric Patients 12 Years and Older When Used with Concomitant Strong or Moderate CYP3A4 Inducers

CYP3A4 Inducers

Avoid concomitant use of strong or moderate CYP3A4 inducers with OXBRYTA [see Drug Interactions (7.1) and Clinical Pharmacology (12.3)].

If concomitant use of strong CYP3A4 inducers is unavoidable, the recommended dosage of OXBRYTA is 2,500 mg orally once daily. If concomitant use of moderate CYP3A4 inducers is unavoidable, the recommended dosage of OXBRYTA is 2,000 mg orally once daily.

2.6 Recommended Dosage of OXBRYTA for Pediatric Patients 4 Years to Less Than 12 Years When Used with Concomitant Strong or Moderate CYP3A4 Inducers

CYP3A4 Inducers

Avoid concomitant use of strong or moderate CYP3A4 inducers with OXBRYTA [see Drug Interactions (7.1) and Clinical Pharmacology (12.3)]. If concomitant use of strong or moderate CYP3A4 inducers is unavoidable, see Table 3 for dosage.

Table 3: OXBRYTA Recommended Dosage for Pediatric Patients 4 Years to Less Than 12 Years When Used with Concomitant Strong or Moderate CYP3A4 Inducers
Body Weight | Recommended Dose (once daily)
Body Weight | Concomitant Use of Strong CYP3A4 Inducers | Concomitant Use of Moderate CYP3A4 Inducers
40 kg or greater | 2,500 mg (five 500 mg tablets) or 2,400 mg (eight 300 mg tablets for oral suspension or eight 300 mg tablets) | 2,000 mg (four 500 mg tablets) or 2,100 mg (seven 300 mg tablets for oral suspension or seven 300 mg tablets)
20 kg to less than 40 kg | 1,500 mg | 1,200 mg
10 kg to less than 20 kg | 900 mg | 900 mg

2.7 Important Administration Instructions

Administer OXBRYTA orally, once daily with or without food. If a dose is missed, or not administered entirely, resume dosing the following day.

OXBRYTA may be given with or without hydroxyurea.

OXBRYTA 300 mg and 500 mg Tablets

Patients should swallow OXBRYTA tablets whole. Do not cut, crush, or chew the tablets.

OXBRYTA 300 mg Tablets for Oral Suspension

Patients should disperse tablets for oral suspension immediately before administration in a cup and in room temperature clear liquid (such as drinking water, clear soda, apple juice, clear electrolyte drinks, clear flavored drinks, or clear sports drinks) before swallowing.

Do not swallow whole, cut, crush, or chew the tablets for oral suspension.

Recommended Daily Dose | Number of Tablets for Oral Suspension | Minimum Recommended Volume of Clear Drink
300 mg | 1 | 5 mL (1 teaspoon)
600 mg | 2 | 10 mL (2 teaspoons)
900 mg | 3 | 15 mL (3 teaspoons)
1,200 mg | 4 | 20 mL (4 teaspoons)
1,500 mg | 5 | 25 mL (5 teaspoons)
2,100 mg | 7 | 35 mL (7 teaspoons)
2,400 mg | 8 | 40 mL (8 teaspoons)

- After the tablets start to disintegrate, swirl the contents of the cup until the tablets are dispersed, wait 1 to 5 minutes, swirl the contents of the cup again, and then orally administer the contents of the cup. The tablet(s) will not completely dissolve; there will still be small tablet clumps in the mixture.
- Resuspend any residue left in the cup in more clear drink and administer. Repeat until no tablet residue is left in the cup.

Tablets for oral suspension may be substituted for tablets in adults and pediatric patients 12 years and older with difficulty swallowing the tablets. Use the number of tablets for oral suspension needed to achieve the recommended dose.

3 DOSAGE FORMS AND STRENGTHS

Tablets: 300 mg light purple to purple, oval shaped, biconvex, debossed with "G 300" on one side.

Tablets: 500 mg light yellow to yellow, oval shaped, biconvex, debossed with "GBT 500" on one side.

Tablets for oral suspension: 300 mg light yellow to yellow, round shaped, debossed with "300 D" on one side.

4 CONTRAINDICATIONS

OXBRYTA is contraindicated in patients with a history of serious drug hypersensitivity reaction to voxelotor or excipients. Clinical manifestations may include generalized rash, urticaria, mild shortness of breath, mild facial swelling, and eosinophilia [see Warnings and Precautions (5.1) and Adverse Reactions (6.1)].

5 WARNINGS AND PRECAUTIONS

5.1 Hypersensitivity Reactions

Serious hypersensitivity reactions after administration of OXBRYTA have occurred in <1% of patients treated. Clinical manifestations may include generalized rash, urticaria, mild shortness of breath, mild facial swelling, and eosinophilia [see Adverse Reactions (6.1)].

Drug reaction with eosinophilia and systemic symptoms (DRESS) has been reported in postmarketing experience with OXBRYTA [see Adverse Reactions (6.2)]. Patients who develop a combination of skin rash, fever, peripheral eosinophilia, and internal systemic organ involvement (e.g., hepatic, renal, pulmonary) while receiving OXBRYTA should undergo medical evaluation.

Advise patients of the signs and symptoms of severe hypersensitivity reactions, including DRESS. If hypersensitivity reactions occur, discontinue OXBRYTA and administer appropriate medical therapy. Do not reinitiate OXBRYTA in patients who experience these symptoms with previous use.

5.2 Laboratory Test Interference

OXBRYTA administration may interfere with measurement of Hb subtypes (HbA, HbS, and HbF) by high-performance liquid chromatography (HPLC) [see Drug Interactions (7.3)]. If precise quantitation of Hb species is required, chromatography should be performed when the patient has not received OXBRYTA therapy in the immediately preceding 10 days.

6 ADVERSE REACTIONS

The following clinically significant adverse reaction is discussed in other sections of the labeling:

- Hypersensitivity Reactions [see Contraindications (4) and Warnings and Precautions (5.1)].

6.1 Clinical Trials Experience

Because clinical trials are conducted under widely varying conditions, adverse reaction rates observed in the clinical trials of a drug cannot be directly compared to rates in the clinical trials of another drug and may not reflect the rates observed in practice.

Adults and Pediatric Patients 12 Years and Older

The safety of OXBRYTA was evaluated in the HOPE trial based on data from 88 patients with SCD who received OXBRYTA 1,500 mg and 91 patients who received placebo orally once daily [see Clinical Studies (14.1)]. Seventy-four patients received OXBRYTA 1,500 mg once daily for ≥24 weeks, 65 patients for ≥48 weeks, and 63 patients completed the 72-week treatment period.

In patients who received OXBRYTA 1,500 mg once daily the median age was 24 years (range:12 to 59 years); 65% female; 66% Black or African American and 23% Arab/Middle Eastern; and 65% receiving hydroxyurea at baseline.

Serious adverse reactions occurred in 3% (3/88) of patients receiving OXBRYTA 1,500 mg, which included headache, drug hypersensitivity, and pulmonary embolism occurring in 1 patient each. Permanent discontinuation due to an adverse reaction (Grades 1-4) occurred in 5% (4/88) of patients who received OXBRYTA 1,500 mg.

Dosage modifications (dose reduction or dosing interruption) due to adverse reactions occurred in 14% (12/88) of patients who received OXBRYTA 1,500 mg. The adverse reactions requiring dosage modification included rash (4.5%), diarrhea (3.4%), headache (2.3%), nausea (2.3%), abdominal pain (1.1%), and drug hypersensitivity (1.1%).

The safety profile observed in pediatric patients 12 to <17 years treated with OXBRYTA in the HOPE trial was similar to that seen in adult patients.

The most common adverse reactions occurring in ≥10% of patients treated with OXBRYTA 1,500 mg with a difference of >3% compared to placebo are summarized in Table 4.

Table 4: Adverse Reactions (≥10%) in Patients Receiving OXBRYTA with a Difference Between Arms of >3% Compared to Placebo in HOPE
Adverse Reaction [Adverse reactions were Grades 1 or 2 except for Grade 3 headache (2), diarrhea (1), nausea (1), rash (1), and rash generalized (3)] | OXBRYTA 1,500 mg (N=88) | Placebo (N=91)
Headache | 32% | 25%
Diarrhea | 23% | 11%
Abdominal Pain [Abdominal pain (grouped PTs) includes the following PTs: abdominal pain, lower abdominal pain, and upper abdominal pain] | 23% | 16%
Nausea | 19% | 10%
Rash [Rash (grouped PTs) includes the following PTs: rash, urticaria, generalized rash, macular rash, maculo-papular rash, pruritic rash, and papular rash] | 15% | 11%
Pyrexia | 15% | 8%

Clinically relevant adverse reactions occurring in <10% of patients included:

- Drug hypersensitivity

Pediatric Patients 4 to <12 Years

The safety of OXBRYTA in pediatric patients 4 to <12 years with SCD was evaluated in an open-label, Phase 2 study [see Clinical Studies (14.2)]. In this study, 45 patients 4 to <12 years of age received doses of OXBRYTA tablets for oral suspension based on weight at baseline. Thirty-five patients received OXBRYTA for 24 weeks and 26 patients for 48 weeks. The most common adverse reactions (>10%) reported in pediatric patients 4 to <12 years were pyrexia (36%), vomiting (33%), rash (20%), abdominal pain (18%), diarrhea (18%), and headache (18%).

The overall safety profile of OXBRYTA in pediatric patients 4 to <12 years was similar to that seen in adults and pediatric patients 12 years and older.

6.2 Postmarketing Experience

The following adverse reactions have been identified during postapproval use of OXBRYTA. Because these reactions are reported voluntarily from a population of uncertain size, it is not always possible to reliably estimate their frequency or establish a causal relationship to drug exposure:

- Drug reaction with eosinophilia and systemic symptoms (DRESS), Pruritis, Angioedema (including swelling of eyelid, face edema, lip swelling, and periorbital swelling).

7 DRUG INTERACTIONS

7.1 Effect of Other Drugs on Voxelotor

Strong or Moderate CYP3A4 Inducers

Coadministration of strong or moderate CYP3A4 inducers may decrease voxelotor plasma and whole blood concentrations and may lead to reduced efficacy.

Avoid coadministration of OXBRYTA with strong or moderate CYP3A4 inducers. Increase the OXBRYTA dosage when coadministration with a strong or moderate CYP3A4 inducer is unavoidable [see Dosage and Administration (2.5, 2.6) and Clinical Pharmacology (12.3)].

7.2 Effect of Voxelotor on Other Drugs

Voxelotor increased the systemic exposure of midazolam (a sensitive CYP3A4 substrate) [see Clinical Pharmacology (12.3)]. Avoid coadministration of OXBRYTA with sensitive CYP3A4 substrates with a narrow therapeutic index. If concomitant use is unavoidable, consider dose reduction of the sensitive CYP3A4 substrate(s).

7.3 Laboratory Test Interference

OXBRYTA administration may interfere with measurement of Hb subtypes (HbA, HbS, and HbF) by HPLC [see Warnings and Precautions (5.2)]. If precise quantitation of Hb species is required, chromatography should be performed when the patient has not received OXBRYTA therapy in the immediately preceding 10 days.

8 USE IN SPECIFIC POPULATIONS

8.1 Pregnancy

Risk Summary

There are no available data on OXBRYTA use in pregnant women to evaluate for a drug-associated risk of major birth defects, miscarriage, or adverse maternal or fetal outcomes. In animal reproduction studies, oral administration of voxelotor to pregnant rats and rabbits during organogenesis at exposures up to 2.8-times (rats) and 0.3-times (rabbits) the exposure at the maximum recommended human dose resulted in no adverse developmental effects (see Data).

The estimated background risk of major birth defects and miscarriage for the indicated population is approximately 14% and up to 43%, respectively. All pregnancies have a background risk of birth defect, loss, or other adverse outcomes.

There are adverse effects on maternal and fetal outcomes associated with SCD in pregnancy (see Clinical Considerations). OXBRYTA should only be used during pregnancy if the benefit of the drug outweighs the potential risk.

Clinical Considerations

Disease-Associated Maternal and/or Embryo/Fetal Risk

Women with SCD have an increased risk of adverse pregnancy outcomes for the mother and the fetus. Pregnant women are at greater risk for vasoocclusive crises, pre-eclampsia, eclampsia, and maternal mortality. For the fetus, there is an increased risk for intrauterine growth restriction, preterm delivery, low birth weight, and perinatal mortality.

Data

Animal Data

In embryo-fetal development studies, voxelotor was administered orally to pregnant rats at 15, 50, and 250 mg/kg/day (gestation days 7 through 17) and rabbits at 25, 75, and 150 mg/kg/day (gestation days 7 through 19) through organogenesis. Maternal toxicity was observed at the highest dose levels in these studies equivalent to 2.8-times (rats) and 0.3-times (rabbits) the exposures in patients receiving OXBRYTA at the recommended daily dose. There was no evidence of adverse developmental outcomes in rats or rabbits.

In a pre- and postnatal development study, voxelotor was administered orally to pregnant rats at 15, 50 and 250 mg/kg/day (gestation day 6 through lactation day 20). Maternal gestational body weights were decreased at 250 mg/kg/day, which continued to the end of lactation. The findings in offspring included reduced survival and reduced body weights throughout lactation, weaning and maturation. The effects in offspring were observed at the maternal dose of 250 mg/kg/day with an exposure approximately 2.8-times the exposure in patients at the recommended dose.

8.2 Lactation

Risk Summary

There are no data on the presence of voxelotor in human milk, the effects on the breastfed child, or the effects on milk production. Voxelotor was detected in milk in lactating rats. Plasma concentrations of voxelotor in pregnant rats were higher than the concentration in milk. When a drug is present in animal milk, it is likely that the drug will be present in human milk. The concentration of voxelotor in animal milk does not necessarily predict the concentration of drug in human milk. Because of the potential for serious adverse reactions in the breastfed child, including changes in the hematopoietic system, advise patients that breastfeeding is not recommended during treatment with OXBRYTA, and for at least 2 weeks after the last dose.

8.4 Pediatric Use

The safety and effectiveness of OXBRYTA for SCD have been established in pediatric patients aged 4 years and older. The safety and efficacy of OXBRYTA in pediatric patients with SCD below the age of 4 years have not been established.

Use of OXBRYTA in pediatric patients 12 to <17 years for SCD is supported by evidence from an adequate and well-controlled study in adults and pediatric patients (HOPE trial). The HOPE trial enrolled 26 pediatric patients aged 12 to <17 years, in which 12 pediatric patients received OXBRYTA 1,500 mg once daily and 14 pediatric patients received OXBRYTA 900 mg once daily [see Adverse Reactions (6.1), Clinical Pharmacology (12.3), and Clinical Studies (14.1)].

Use of OXBRYTA in pediatric patients 4 to <12 years for SCD is supported by evidence from an open-label, Phase 2 study. The study enrolled 45 pediatric patients aged 4 to <12 years and 11 patients aged 12 to <17 years with SCD. Patients 12 to <17 years received OXBRYTA 1,500 mg once daily. Patients 4 to <12 years were administered OXBRYTA based on body weight. OXBRYTA doses of 600 mg, 900 mg, or 1,500 mg once daily were administered to patients weighing 10 kg to <20 kg, 20 kg to <40 kg, or ≥40 kg, respectively [see Adverse Reactions (6.1), Clinical Pharmacology (12.3), and Clinical Studies (14.2)].

Pharmacokinetics, safety and efficacy were similar across the pediatric age groups and across pediatric and adult patients [see Dosage and Administration (2), Clinical Pharmacology (12.3) and Clinical Studies (14)].

The adverse reactions observed were similar across the pediatric age groups and across pediatric and adult patients [see Adverse Reactions (6.1)].

8.5 Geriatric Use

Clinical studies of OXBRYTA did not include sufficient numbers of subjects aged 65 and over to determine whether they respond differently from younger subjects.

8.6 Hepatic Impairment

Severe hepatic impairment increases voxelotor exposures [see Clinical Pharmacology (12.3)]. Reduce OXBRYTA dose [see Dosage and Administration (2.3, 2.4)].

11 DESCRIPTION

OXBRYTA contains voxelotor, a hemoglobin S polymerization inhibitor. The chemical name of voxelotor is 2-hydroxy-6-((2-(1-isopropyl-1H-pyrazol-5-yl)pyridin-3-yl)methoxy)benzaldehyde with a molecular formula of C19H19N3O3 and a molecular weight of 337.4.

The chemical structure of voxelotor is:

Voxelotor is a white-to-yellow-to-beige compound in crystalline Form II of its free base. It is non-hygroscopic and highly soluble in common organic solvents such as acetone and toluene and insoluble in water.

OXBRYTA film-coated tablets for oral use contain either 300 mg or 500 mg of voxelotor. Both strengths of OXBRYTA film-coated tablets contain the following inactive ingredients: colloidal silicon dioxide, croscarmellose sodium, magnesium stearate, microcrystalline cellulose, and sodium lauryl sulfate. In addition, the 500 mg tablet film coating contains: polyethylene glycol 3350, polyvinyl alcohol, talc, titanium dioxide, and yellow iron oxide. The 300 mg tablet film coating contains: black and red iron oxide, polyethylene glycol 3350, polyvinyl alcohol, talc, and titanium dioxide.

Each OXBRYTA tablet for oral suspension contains 300 mg of voxelotor with the following inactive ingredients: artificial grape flavor, colloidal silicon dioxide, croscarmellose sodium, iron oxide pigment, magnesium stearate, microcrystalline cellulose, and sucralose.

12 CLINICAL PHARMACOLOGY

12.1 Mechanism of Action

Voxelotor is a hemoglobin S (HbS) polymerization inhibitor that binds to HbS with a 1:1 stoichiometry and exhibits preferential partitioning to red blood cells (RBCs). By increasing the affinity of Hb for oxygen, voxelotor demonstrates dose-dependent inhibition of HbS polymerization. Nonclinical studies suggest that voxelotor may inhibit RBC sickling, improve RBC deformability, and reduce whole blood viscosity.

12.2 Pharmacodynamics

The pharmacodynamic effect of voxelotor treatment demonstrated a dose-dependent increase in Hb oxygen affinity as determined by the change in p50 (partial pressure of oxygen at which Hb oxygen saturation of 50% is achieved) that was linearly correlated with voxelotor exposure.

The pharmacodynamic effect of voxelotor treatment also demonstrated a dose-dependent reduction in clinical measures of hemolysis (indirect bilirubin and % reticulocytes).

Cardiac Electrophysiology

At plasma concentrations approximately 2-fold above therapeutic concentrations, voxelotor does not prolong QT interval to any clinically relevant extent.

12.3 Pharmacokinetics

Voxelotor is absorbed into plasma and is then distributed predominantly into RBCs due to its preferential binding to Hb. The major route of elimination of voxelotor is by metabolism with subsequent excretion of metabolites into urine and feces. The PK are linear and voxelotor exposures increased proportionally with either single or multiple doses (Table 5) in whole blood, plasma, and RBCs. Steady-state after repeated administration is reached within 8 days and exposures of voxelotor are consistent with accumulation predicted based on single dose data in patients with SCD.

Table 5: Pharmacokinetics Parameters of Voxelotor in Plasma and Whole Blood [Based on the 72-week population pharmacokinetic analysis.]
PK Parameter | Voxelotor 1,500 mg Geometric Mean (%CV)
Plasma PK
AUC0-24h (μg∙hr/mL) | 278 (28.4)
Cmax (µg/mL) | 14 (24.5)
Half-life (hours) | 38.7 (30.2)
Whole Blood PK
AUC0-24h (μg∙hr/mL) | 3,830 (33.5)
Cmax (µg/mL) | 180 (31)

In healthy subjects, voxelotor exposures were comparable when administered as tablet for oral suspension dispersed in water or as oral tablet swallowed whole.

Absorption

The median plasma and whole blood Tmax of voxelotor after oral administration is 2 hours. The mean peak concentrations in whole blood and RBCs are observed between 6 and 18 hours after oral administration.

Effect of Food

A high-fat, high-calorie meal increased voxelotor AUC by 42% and Cmax by 45% in whole blood relative to AUC and Cmax in the fasted state. Similarly, AUC increased by 42% and Cmax increased by 95% in plasma.

Distribution

Voxelotor apparent volume of distribution of the central compartment and peripheral compartment are 333 L and 72.3 L in plasma, respectively. Protein binding is 99.8% in vitro. The blood-to-plasma ratio is approximately 17:1 in patients with SCD.

Elimination

The geometric mean (%CV) terminal elimination half-life of voxelotor in patients with SCD is 38.7 hours (30.2%) with concentrations in plasma, whole blood, and RBCs declining in parallel. The apparent oral clearance of voxelotor was estimated as 6.1 L/h in plasma in patients with SCD.

Metabolism

In vitro and in vivo studies indicate that voxelotor is extensively metabolized through Phase I (oxidation and reduction), Phase II (glucuronidation) and combinations of Phase I and II metabolism. Metabolism of voxelotor is mediated by CYP3A4, CYP3A5, CYP2B6, CYP2C19, CYP2C9, UGT1A1, and UGT1A9.

Excretion

Following the administration of radiolabeled voxelotor, approximately 62.6% of the dose and its metabolites are excreted into feces (33.3% unchanged) and 35.5% in urine (0.08% unchanged).

Specific Populations

No clinically significant differences in the pharmacokinetics of voxelotor were observed based on age (12 to 59 years), sex, body weight (28 to 135 kg), or mild to severe renal impairment (creatinine clearance [CLcr] 15-89 mL/min).

Pediatric Patients

The pharmacokinetic exposures of voxelotor in whole blood and plasma were similar between pediatric patients 4 to <17 years and adults following the recommended dosage [see Dosage and Administration (2)].

Patients with Renal Impairment

There was no clinically significant effect of renal function on the excretion of voxelotor. Following a single 900 mg dose of voxelotor, whole blood exposures in subjects with severe renal impairment (eGFR <30 mL/min/1.73 m^2) were 25% lower compared to healthy controls.

The unbound plasma concentrations were comparable. OXBRYTA has not been evaluated in patients with end stage renal disease requiring dialysis.

Patients with Hepatic Impairment

The voxelotor AUC in whole blood were 14% and 15% higher in subjects with mild and moderate hepatic impairment (Child Pugh A and B) and 90% higher in subjects with severe hepatic impairment (Child Pugh C) compared to subjects with normal hepatic function.

Patients with HbSC Genotype

Voxelotor steady state whole blood AUC and Cmax were 50% and 45% higher in HbSC genotype patients (n=11) compared to HbSS genotype (n=220) patients and voxelotor steady state plasma AUC and Cmax were 23% and 15% higher in HbSC genotype patients compared to HbSS genotype patients.

Drug Interaction Studies

Clinical Studies and Model-Informed Approaches

Effect of Strong CYP3A4 Inhibitors on Voxelotor: concomitant use of OXBRYTA with itraconazole increased voxelotor AUC in healthy subjects by 11%.

Effect of Strong or Moderate CYP3A4 Inducers on Voxelotor: concomitant use of OXBRYTA with rifampin (a strong CYP3A4 inducer) is predicted to decrease voxelotor AUC in patients by up to 40%, and efavirenz (a moderate CYP3A4 inducer) is predicted to decrease voxelotor AUC in patients by up to 24%.

Effect of Acid Reducing Agents on Voxelotor: coadministration of omeprazole (proton pump inhibitor) with OXBRYTA did not alter voxelotor exposure.

Effect of Voxelotor on CYP450 Enzymes: in vivo voxelotor inhibits CYP3A4, but not CYP1A2, CYP2C9, CYP2C19, CYP2C8, or CYP2D6. The observed exposure increase of the CYP3A4 substrate midazolam in healthy subjects was 1.6-fold and the predicted increase in patients after multiple dosing is 2.5-fold.

Effect of Voxelotor on P-gp: concomitant use of OXBRYTA with digoxin (a P-gp substrate) did not alter digoxin to a clinically relevant extent.

In Vitro Studies

CYP Enzymes: voxelotor is a reversible and time-dependent inhibitor as well as an inducer of CYP2B6.

Transporter Systems: voxelotor is not an inhibitor of P-gp, BCRP, OATP1B1, OATP1B3, OCT2, OAT1, OAT3, MATE1, MATE2-K, or BSEP. Voxelotor is not a substrate of P-gp, BCRP, OATP1A2, OATP1B1, OATP1B3, or BSEP.

13 NONCLINICAL TOXICOLOGY

13.1 Carcinogenesis, Mutagenesis, Impairment of Fertility

Voxelotor was not carcinogenic in a 26-week study in RasH2 transgenic mice at oral doses of 30, 150, or 500 mg/kg/day.

Voxelotor was not genotoxic in the reverse mutation bacterial (Ames) test, rat Comet assay, or rat micronucleus assay.

In a fertility and early embryonic development study, voxelotor was administered orally to rats at 15, 50, and 250 mg/kg/day. Males were dosed 28 days prior to mating through cohabitation and females were dosed 14 days prior to mating through gestation Day 7. Voxelotor had no effect on fertility or reproductive function. Sperm motility was decreased and changes in sperm morphology occurred at 250 mg/kg/day (approximately 5-times the human exposure at 1,500 mg/day).

14 CLINICAL STUDIES

14.1 Adults and Pediatric Patients 12 Years and Older

The efficacy and safety of OXBRYTA in SCD was evaluated in HOPE, a Phase 3 randomized, double-blind, placebo-controlled, multicenter trial [NCT 03036813]. In this study, 274 patients were randomized to daily oral administration of OXBRYTA 1,500 mg (N=90), OXBRYTA 900 mg (N=92), or placebo (N=92). Patients were included if they had from 1 to 10 vasoocclusive crisis (VOC) events within 12 months prior to enrollment and baseline hemoglobin (Hb) ≥5.5 to ≤10.5 g/dL. Eligible patients on stable doses of hydroxyurea for at least 90 days were allowed to continue hydroxyurea therapy throughout the study. Randomization was stratified by patients already receiving hydroxyurea (yes, no), geographic region (North America, Europe, Other), and age (12 to <17 years, 18 to 65 years). The trial excluded patients who received red blood cell (RBC) transfusions within 60 days and erythropoietin within 28 days of enrollment, had renal insufficiency, uncontrolled liver disease, were pregnant, or lactating.

The majority of patients had HbSS or HbS/beta^0-thalassemia genotype (90%) and were receiving background hydroxyurea therapy (65%). The median age was 24 years (range: 12 to 64 years); 46 (17%) patients were 12 to <17 years. Median baseline Hb was 8.5 g/dL (5.9 to 10.8 g/dL). One hundred and fifteen (42%) had 1 VOC event and 159 (58%) had 2 to 10 events within 12 months prior to enrollment. In the OXBRYTA 1,500 mg group, 63 (70%) patients completed the study through Week 72.

Efficacy was based on Hb response rate defined as a Hb increase of >1 g/dL from baseline to Week 24 in patients treated with OXBRYTA 1,500 mg versus placebo. The response rate for OXBRYTA 1,500 mg was 51.1% (46/90) compared to 6.5% (6/92) in the placebo group (p < 0.001). No outlier subgroups were observed. The distribution of Hb change from baseline for individual patients completing 24 weeks of treatment with OXBRYTA 1,500 mg or placebo is depicted in Figure 1.

Figure 1: Subject-level Change from Baseline in Hemoglobin at Week 24 in Patients Who Completed 24 Weeks of Treatment [Approximately 83% of all randomized patients completed 24 weeks of treatment.]

Additional efficacy evaluation included change in Hb and percent change in indirect bilirubin and percent reticulocyte count from baseline to Week 24 (Table 6).

Table 6: Adjusted Mean (SE) Change from Baseline to Week 24 in Hemoglobin and Clinical Measures of Hemolysis
 | OXBRYTA 1,500 mg QD (N=90) | Placebo (N=92) | P Value
Hemoglobin | 1.1 g/dL (0.1) | -0.1 g/dL (0.1) | < 0.001
Indirect Bilirubin | -29.1% (3.5) | -2.8% (3.5) | < 0.001
Percent Reticulocyte Count | -18.0% (4.7) | 6.8% (4.7) | < 0.001
QD = once daily; SE = standard error

14.2 Pediatric Patients 4 to <12 Years

The efficacy and safety of OXBRYTA in patients 4 to <12 years with SCD was evaluated in an open-label, multi-center, Phase 2 trial [NCT 02850406]. In this study, 45 patients 4 to <12 years and 11 patients 12 to <17 years received OXBRYTA. Patients 4 to <12 years received tablets for oral suspension based on body weight at baseline. OXBRYTA doses of 600 mg, 900 mg, or 1,500 mg once daily were administered to patients weighing 10 kg to <20 kg, 20 kg to <40 kg, or ≥40 kg, respectively. Patients 12 to <17 years received OXBRYTA 1,500 mg once daily.

Patients were included if their baseline hemoglobin (Hb) was ≤10.5 g/dL. Eligible patients on stable doses of hydroxyurea for at least 90 days were allowed to continue hydroxyurea therapy throughout the study. The trial excluded patients who had a VOC event within 14 days prior to enrollment, received red blood cell (RBC) transfusions within 30 days of enrollment, and had renal insufficiency or uncontrolled liver disease.

All patients had HbSS or HbS/beta^0-thalassemia genotype (100%) and most were receiving background hydroxyurea therapy (80%). The median age was 8 years (range: 4 to 15 years); 45 (80%) patients were 4 to <12 years. In this age group, mean baseline Hb was 8.6 g/dL (range: 6.1 to 10.5 g/dL).

Efficacy was based on Hb response rate, which is defined as a Hb increase of >1 g/dL from baseline to Week 24. Hb response rate for OXBRYTA in patients aged 4 to <12 years who took at least one dose of OXBRYTA was 36% (16/45) (95% CI: 21.6%, 49.5%).

16 HOW SUPPLIED/STORAGE AND HANDLING

The 300 mg tablet is film-coated, light purple to purple, oval shaped, biconvex, debossed with "G 300" on one side, available in:

- Bottles of 60 tablets with one desiccant canister, a polyester coil and child-resistant closure: NDC 72786-102-02
- Bottles of 90 tablets with one desiccant canister, a polyester coil and child-resistant closure: NDC 72786-102-03

The 500 mg tablet is film-coated, light yellow to yellow, oval shaped, biconvex, debossed with "GBT 500" on one side, and available in:

- Bottles of 90 tablets with one desiccant canister, a polyester coil and child-resistant closure: NDC 72786-101-01

The 300 mg tablet for oral suspension is light yellow to yellow, round shaped, debossed with "300 D" on one side, and available in:

- Bottles of 60 tablets for oral suspension with a polyester coil and child-resistant closure: NDC 72786-111-02
- Bottles of 90 tablets for oral suspension with a polyester coil and child-resistant closure: NDC 72786-111-03

Do not eat the desiccant canister or the polyester coil.

STORAGE AND HANDLING

Store OXBRYTA at 20°C to 30°C (68°F to 86°F).

17 PATIENT COUNSELING INFORMATION

Advise the patient to read the FDA-approved patient labeling (Patient Information and Instructions for Use).

Hypersensitivity Reactions

Advise patients that serious hypersensitivity reactions including DRESS may occur, and to notify their healthcare providers if they develop generalized rash, urticaria, shortness of breath, facial swelling, swelling around their eyes, lips, or tongue, fever, fatigue, muscle and/or joint pain, swollen glands, and eosinophilia [see Warnings and Precautions (5.1)]. Inform patients that some severe hypersensitivity reactions may affect their internal organs (such as liver, kidneys, lungs) and their blood cells. Advise patients to stop OXBRYTA if a severe hypersensitivity reaction is suspected.

Breastfeeding

Advise women not to breastfeed while they are on OXBRYTA therapy [see Use in Specific Populations (8.2)].

Dosage and Administration

To avoid a dosing error from using the wrong formulation of OXBRYTA, strongly advise patients and caregivers to visually inspect the tablets to verify the correct formulation each time the prescription is filled [see Dosage and Administration (2) and How Supplied/Storage and Handling (16)].

Advise patients to:

- Store OXBRYTA at 20°C to 30°C (68°F to 86°F).
- Continue taking OXBRYTA every day for as long as their physician tells them.
- Do not take St John's wort while taking OXBRYTA.
- Swallow OXBRYTA tablets whole. Do not cut, crush, or chew the tablets.
- Do not swallow whole, cut, crush, or chew OXBRYTA tablets for oral suspension. Disperse OXBRYTA tablets for oral suspension in room temperature clear drink (such as drinking water, clear soda, apple juice, clear electrolyte drinks, clear flavored drinks, or clear sports drinks) before administration. The amount of liquid needed to disperse the tablets for oral suspension will depend on the dose (number of tablets prescribed) [see Dosage and Administration (2.7)].
- Take OXBRYTA with or without food.
- If a dose is missed or not consumed entirely, resume dosing the following day [see Dosage and Administration (2.7)].

This product's label may have been updated. For most recent prescribing information, please visit www.pfizer.com. For medical information about OXBRYTA, please visit www.pfizermedinfo.com or call 1-800-438-1985.

Distributed by
Global Blood Therapeutics, Inc
A subsidiary of Pfizer Inc.
South San Francisco, CA 94080

LAB-1554-1.0

PATIENT INFORMATION

OXBRYTA® (ox brye ta)
(voxelotor)
tablets

OXBRYTA® (ox brye ta)
(voxelotor)
tablets for oral suspension

What is OXBRYTA?
OXBRYTA is a prescription medicine used for the treatment of sickle cell disease in adults and children 4 years of age and older.
It is not known if OXBRYTA is safe and effective in children with sickle cell disease below 4 years of age.

Do not take OXBRYTA if you or your child have had an allergic reaction to voxelotor or any of the ingredients in OXBRYTA. See the end of this leaflet for a list of the ingredients in OXBRYTA.

Before taking OXBRYTA, tell your healthcare provider about all of your medical conditions, including if you or your child:

- have liver problems
- are pregnant or plan to become pregnant. It is not known if OXBRYTA can harm your unborn baby.
- are breastfeeding or plan to breastfeed. It is not known if OXBRYTA can pass into your breastmilk and if it can harm your baby. Do not breastfeed during treatment with OXBRYTA and for at least 2 weeks after the last dose.

Tell your healthcare provider about all the medicines you or your child take, including prescription and over-the-counter medicines, vitamins, and herbal supplements. Some medicines may affect how OXBRYTA works. OXBRYTA may also affect how other medicines work and may affect the results of certain blood tests. Keep a list of all your medicines and show it to your healthcare provider.

How should I take OXBRYTA?

- Take OXBRYTA exactly as your healthcare provider tells you.
- Do not change your dose or stop taking OXBRYTA unless your healthcare provider tells you to. Your healthcare provider may change your dose if needed.
- Take your prescribed dose of OXBRYTA 1 time each day.
- Take OXBRYTA with or without food.
- OXBRYTA comes in two different dosage forms, OXBRYTA tablets and OXBRYTA tablets for oral suspension. Your healthcare provider will decide which dosage form you take based on your age, weight, and ability to swallow tablets.
  - If you take OXBRYTA tablets: Swallow each OXBRYTA tablet whole. Do not cut, crush, or chew the tablets.
  - If you take OXBRYTA tablets for oral suspension: See the detailed Instructions for Use on how to prepare and take your dose. You must mix the OXBRYTA tablets for oral suspension in room temperature clear drink, such as drinking water, clear soda, apple juice, clear electrolyte drinks, clear flavored drinks, or clear sports drinks, right before taking it. Do not swallow whole, cut, crush, or chew the tablets for oral suspension.
- Check to make sure you receive the correct dosage form of OXBRYTA each time your prescription is filled to avoid taking the wrong medicine.
- Your healthcare provider may also prescribe a medicine called hydroxyurea during treatment with OXBRYTA.
- If you or your child miss a dose of OXBRYTA or if the entire dose is not taken, skip that dose and return to your normal dosing schedule the next day.

What should I avoid while taking OXBRYTA?
Do not take St. John's wort during treatment with OXBRYTA.

What are the possible side effects of OXBRYTA?
OXBRYTA can cause serious side effects, including:

- Severe skin rash and serious allergic reactions. Treatment with OXBRYTA may cause severe skin reactions and serious allergic reactions. The organs in your body may also be affected, such as your liver, kidneys or lungs, and your blood cells.
- Stop taking OXBRYTA, and tell your healthcare provider or get emergency medical help right away if you develop any of the following signs or symptoms during treatment:

- rash
- hives
- high temperature (fever)
- swollen glands (lymph nodes)
- trouble swallowing

- shortness of breath (difficult breathing)
- swelling of your face, around your eyes, lips, or tongue
- lack of energy and tiredness (fatigue)
- muscle or joint aches

The most common side effects of OXBRYTA include:

- headache
- diarrhea
- stomach-area (abdominal) pain

- nausea
- rash or hives
- fever

The most common side effects of OXBRYTA in children ages 4 to less than 12 years of age include:

- fever
- vomiting
- rash

- stomach-area (abdominal) pain
- diarrhea
- headache

These are not all the possible side effects of OXBRYTA.
Call your doctor for medical advice about side effects. You may report side effects to FDA at 1-800-FDA-1088.
You may also report side effects to Pfizer Inc. at 1-800-438-1985.

How should I store OXBRYTA?

- Store OXBRYTA between 68°F to 86°F (20°C to 30°C).
- The OXBRYTA bottle comes with a child-resistant closure.
- The OXBRYTA bottle may contain a desiccant canister to help keep your medicine dry (protect it from moisture) and a polyester coil. Do not eat the desiccant or polyester coil.

Keep OXBRYTA and all medicines out of the reach of children.

General information about the safe and effective use of OXBRYTA.
Medicines are sometimes prescribed for purposes other than those listed in a Patient Information leaflet. Do not use OXBRYTA for a condition for which it was not prescribed. Do not give OXBRYTA to other people, even if they have the same symptoms that you have. It may harm them. You can ask your pharmacist or healthcare provider for information about OXBRYTA that is written for health professionals.

What are the ingredients of OXBRYTA?
Active Ingredient: voxelotor
Inactive Ingredients:
OXBRYTA tablets: colloidal silicon dioxide, croscarmellose sodium, magnesium stearate, microcrystalline cellulose, and sodium lauryl sulfate. The 500 mg tablet film coating contains: polyethylene glycol 3350, polyvinyl alcohol, talc, titanium dioxide, and yellow iron oxide. The 300 mg tablet film coating contains: black and red iron oxide, polyethylene glycol 3350, polyvinyl alcohol, talc, and titanium dioxide.
OXBRYTA tablets for oral suspension: artificial grape flavor, colloidal silicon dioxide, croscarmellose sodium, iron oxide pigment, magnesium stearate, microcrystalline cellulose, and sucralose.

Distributed by

Global Blood Therapeutics, Inc

A subsidiary of Pfizer Inc.

South San Francisco, CA 94080
LAB-1567-1.0

For more information, go to www.pfizer.com or call 1-800-438-1985.

This Patient Information has been approved by the U.S. Food and Drug Administration

Revised: 08/2023

INSTRUCTIONS FOR USE
OXBRYTA® [ox brye ta]
(voxelotor)
tablets for oral suspension
300 mg
This Instructions for Use contains information on how to take OXBRYTA tablets for oral suspension.
Read this Instructions for Use before you or your child start taking OXBRYTA tablets for oral suspension for the first time and each time you or your child get a refill. There may be new information. This information does not take the place of talking to your healthcare provider about your or your child's medical condition or treatment.
Talk to your healthcare provider or pharmacist if you have questions about how to take or give the prescribed dose of OXBRYTA tablets for oral suspension.
Important Information You Need to Know Before Taking OXBRYTA Tablets for Oral Suspension:
- Take OXBRYTA tablets for oral suspension exactly as your healthcare provider tells you.
- Your healthcare provider will tell you how many OXBRYTA tablets for oral suspension you will need for your or your child's dose.
- OXBRYTA comes in two different dosage forms. Each time you receive your or your child's prescription, check the bottle to make sure that you received the prescribed dosage form of OXBRYTA tablets for oral suspension. OXBRYTA tablets for oral suspension are light yellow to yellow, round shaped, and marked with "300 D" on one side. Contact your pharmacist or healthcare provider if you did not receive the correct dosage form.
- Do not swallow whole, cut, crush, or chew OXBRYTA tablets for oral suspension.
- You must first mix OXBRYTA tablets for oral suspension in room temperature clear drink, such as drinking water, clear soda, apple juice, clear electrolyte drinks, clear flavored drinks, or clear sports drinks, before swallowing.
- If you or your child miss a dose of OXBRYTA tablets for oral suspension or if the entire dose is not taken, skip that dose and return to the normal dosing schedule the next day.
- For more information about OXBRYTA tablets for oral suspension, see the Patient Information leaflet.
Gather supplies
You will need the following items to prepare the dose of OXBRYTA tablets for oral suspension (not included with OXBRYTA tablets for oral suspension):; - a teaspoon - a small cup - room temperature clear drink, such as drinking water, clear soda, apple juice, clear electrolyte drinks, clear flavored drinks, or clear sports drinks.; You will also need:; - the prescribed number of OXBRYTA tablets for oral suspension needed for your dose.
Preparing a dose of OXBRYTA tablets for oral suspension
Step 1. | Wash and dry your hands well before preparing the dose.
Step 2. | Pour room temperature clear drink into the cup. The table below shows the amount of clear drink needed for your prescribed dose. You may add more clear drink if needed to mix the tablets.
 | Number of OXBRYTA Tablets for Oral Suspension | Amount of Clear Drink
 | 1 | 1 teaspoon (5 mL)
 | 2 | 2 teaspoons (10 mL)
 | 3 | 3 teaspoons (15 mL)
 | 4 | 4 teaspoons (20 mL)
 | 5 | 5 teaspoons (25 mL)
 | 7 | 7 teaspoons (35 mL)
 | 8 | 8 teaspoons (40 mL)
Step 3. | Add the prescribed number of OXBRYTA tablets for oral suspension into the cup.
Step 4. | Swirl the cup until the tablet(s) break apart (disperse) in the drink. Be careful not to spill the mixture.; - The tablet(s) will not completely dissolve. You will still see small tablet clumps in the mixture. - If you spill any medicine, clean up the spill. Throw away the rest of the prepared medicine and make a new dose.
Step 5. | Wait for 1 to 5 minutes.
Giving the dose
Step 6. | Swirl the cup again. Take or give all of the prepared medicine right away.; - If giving to a child, make sure that your child is upright when drinking the medicine mixture.
Step 7. | Add 1 or 2 teaspoons of room temperature clear drink to the cup to make sure the full dose is taken. Swirl the cup until the remaining medicine is mixed and take or give it right away.; - Repeat this step until no more medicine is left in the cup. - After all the medicine is taken, you or your child may drink more water or any type of drink.
Step 8. | Wash the teaspoon and cup with warm soap and water.
Storing OXBRYTA
- Store OXBRYTA between 68°F to 86°F (20°C to 30°C).
- The OXBRYTA bottle comes with a child-resistant closure.
- The OXBRYTA tablets for oral suspension bottle contains a polyester coil. Do not eat the polyester coil.
Keep OXBRYTA and all medicines out of the reach of children.
Disposing of OXBRYTA
When all the tablets in the bottle have been taken, throw away the bottle. Safely dispose of (throw away) OXBRYTA that is out of date or no longer needed using your local household waste guidelines.
Distributed by
Global Blood Therapeutics, Inc
A subsidiary of Pfizer Inc.
South San Francisco, CA 94080
LAB-1568-1.0
For more information, go to www.pfizer.com or call 1-800-438-1985.
This Instructions for Use has been approved by the U.S. Food and Drug Administration. |  |  |  | Revised: 08/2023

PRINCIPAL DISPLAY PANEL - 500 mg Tablet Bottle Label

NDC 72786-101-01
Pfizer

Oxbryta®

(voxelotor)
tablets

500 mg

Swallow tablets whole.
Do not cut, crush, or chew the tablets.

90 tablets
Rx only

PRINCIPAL DISPLAY PANEL - 300 mg Tablet Bottle Label

NDC 72786-111-03
Pfizer

Oxbryta®

(voxelotor)
tablets for oral
suspension

300 mg

90 tablets
Rx only

PRINCIPAL DISPLAY PANEL - 300 mg Tablet Bottle Label - 72786-102

NDC 72786-102-03
Rx only

Oxbryta®
(voxelotor) tablets

300 mg

Swallow tablets whole.
Do not cut, crush, or chew the tablets.

90 tablets